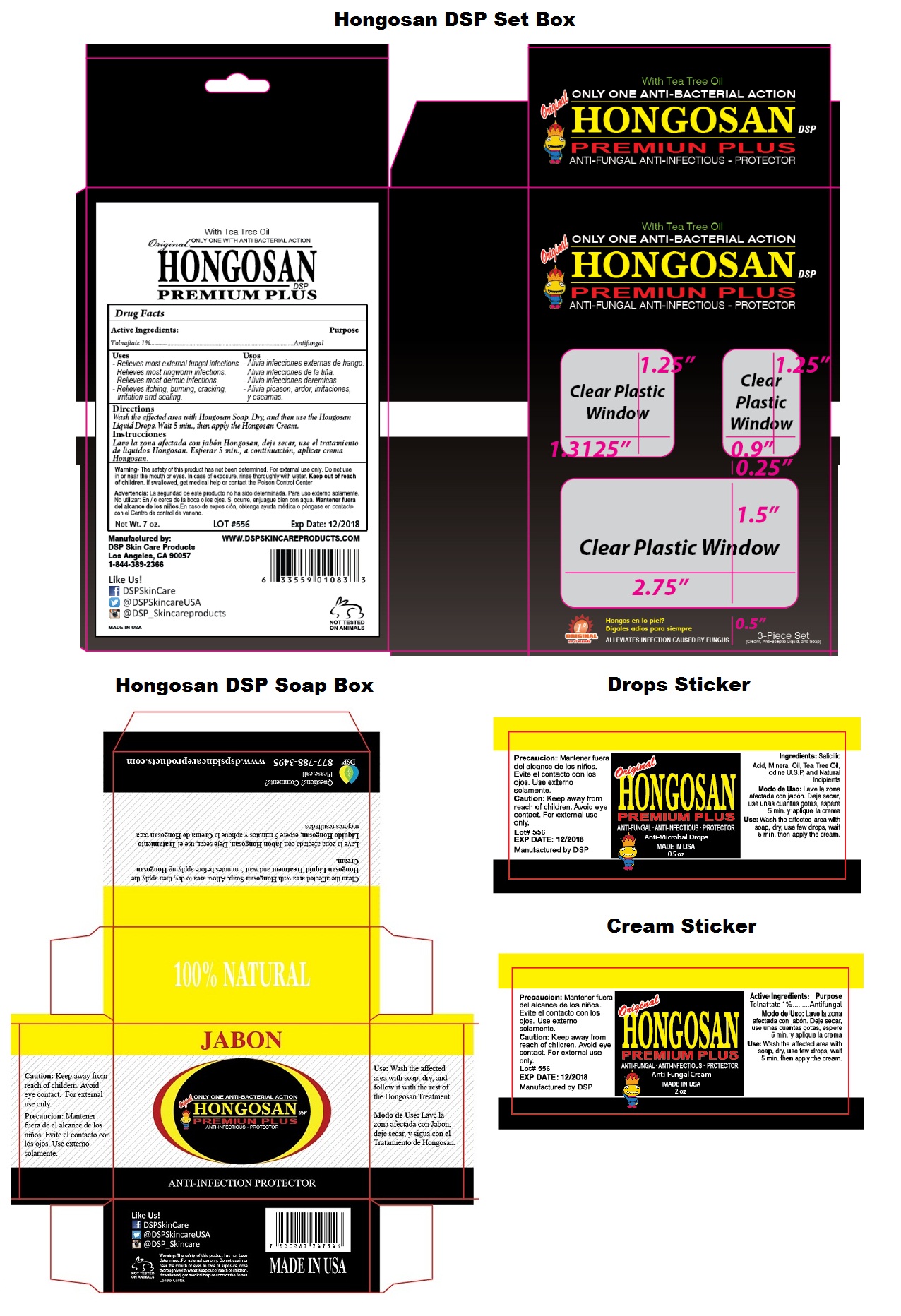 DRUG LABEL: HONGOSAN DSP
NDC: 70826-576 | Form: KIT | Route: TOPICAL
Manufacturer: Dsp Skin Care Products
Category: otc | Type: HUMAN OTC DRUG LABEL
Date: 20160709

ACTIVE INGREDIENTS: TOLNAFTATE 10 mg/1 g
INACTIVE INGREDIENTS: WATER; GLYCERIN; TEA TREE OIL; STEARIC ACID; ISOPROPYL PALMITATE; GLYCOL STEARATE; PEG-100 STEARATE; MINERAL OIL; DIMETHICONE; PETROLATUM; GLYCERYL MONOSTEARATE; PHENOXYETHANOL; CETYL ALCOHOL; METHYLPARABEN; CARBOMER INTERPOLYMER TYPE A (ALLYL SUCROSE CROSSLINKED); TROLAMINE; EDETATE DISODIUM; STEARAMIDE AMP; CEDROL; HYDROXYETHYL UREA

HONGOSAN DSP KIT

Active ingredients:

Tolnaftate 1%

Purpose

Antifungal

Keep out of reach of children. If swallowed, get medical help or contact the Poison Control Center

Uses

- Relieves most external fungal infections.

- Relieves most ringworm infections.

- Relieves most dermic infections.

- Relieves itching, burning, cracking, irritation and scaling.

WARNINGS

Warning- The safety of this product has not been determined. For external use only. Do not use in or near the mouth or eyes. In case of exposure, rinse thoroughly with water.

Directions

Wash the affected area with Hongosan Soap. Dry, and then use the Hongosan Liquid Drops, Wait 5 min., then apply the Hongosan Cream.

Inactive ingredients:

Water, Glycerin, Tea tree oil, Stearic acid, Isopropyl Palmitate, Glycol Stearate, PEG-100 Stearate, Mineral oil, Dimethicone, Petrolatum, Glyceryl Stearate, Phenoxyethanol, Cetyl alcohol, Methylparaben, Acrylates/C10-30 Alkyl Acrylate Crosspolymer, Triethanolamine, Disodium EDTA, Stearamide AMP, Cedrol and Hydroxyethyl Urea.

With Tea Tree Oil

ONLY ONE ANTI-BACTERIAL ACTION

PREMIUM PLUS

ANTI-FUNGAL ANTI-INFECTIOUS - PROTECTOR

3-Piece Set
(Cream, Anti-septic Liquid and Soap)

Manufactured by:
DSP Skin Care Products
Los Angeles, CA 90057
1-844-389-2366